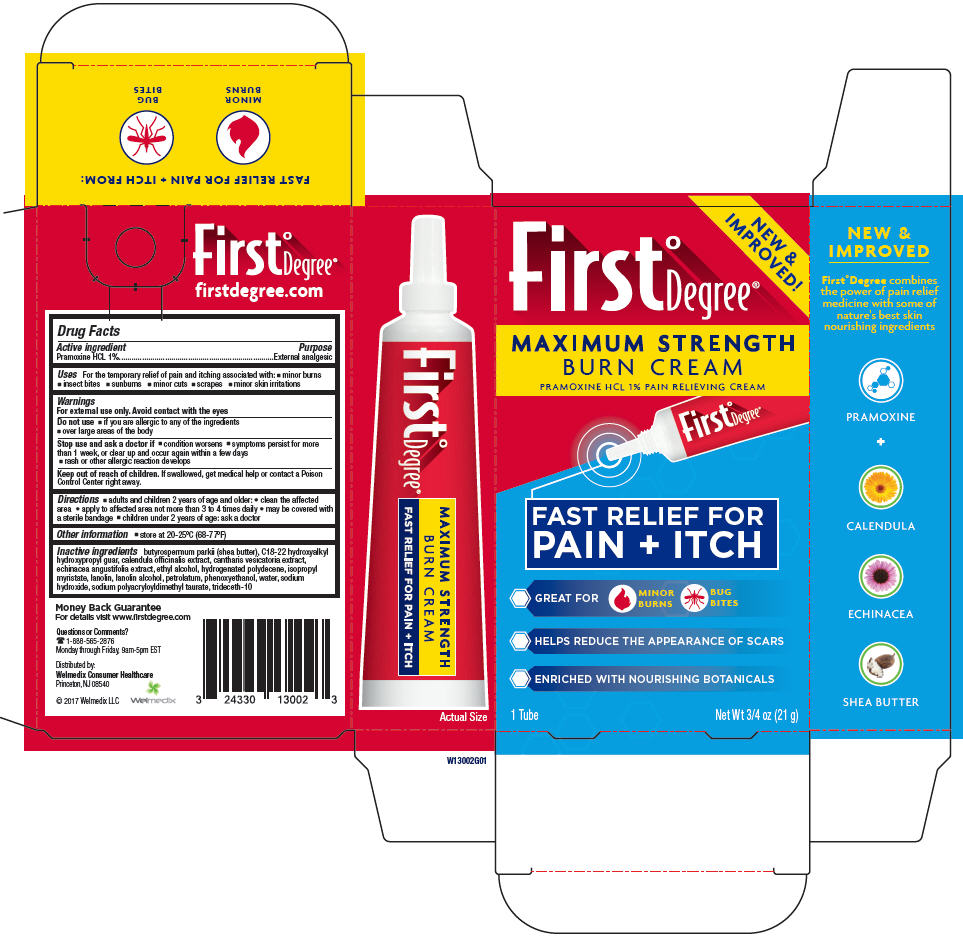 DRUG LABEL: First Degree Maximum Strength Burn
NDC: 24330-130 | Form: CREAM
Manufacturer: Welmedix LLC
Category: otc | Type: HUMAN OTC DRUG LABEL
Date: 20170309

ACTIVE INGREDIENTS: Pramoxine Hydrochloride 10 mg/1 g
INACTIVE INGREDIENTS: SHEA BUTTER; CALENDULA OFFICINALIS FLOWERING TOP; LYTTA VESICATORIA; GUAR GUM; ECHINACEA ANGUSTIFOLIA; ALCOHOL; HYDROGENATED POLYDECENE (550 MW); ISOPROPYL MYRISTATE; LANOLIN; LANOLIN ALCOHOLS; PETROLATUM; PHENOXYETHANOL; WATER; SODIUM HYDROXIDE; SODIUM TAURATE; TRIDECETH-10

First° Degree® Maximum Strength Burn Cream

Drug Facts

Active ingredient

Pramoxine HCL 1%

Purpose

External analgesic

Uses

For the temporary relief of pain and itching associated with:

- minor burns
- insect bites
- sunburns
- minor cuts
- scrapes
- minor skin irritations

Warnings

For external use only. Avoid contact with the eyes

Do not use

- if you are allergic to any of the ingredients
- over large areas of the body

Stop use and ask a doctor if

- condition worsens
- symptoms persist for more than 1 week, or clear up and occur again within a few days
- rash or other allergic reaction develops

Keep out of reach of children. If swallowed, get medical help or contact a Poison Control Center right away.

Directions

- adults and children 2 years of age and older:
  - clean the affected area
  - apply to affected area not more than 3 to 4 times daily
  - may be covered with a sterile bandage
- children under 2 years of age: ask a doctor

Other information

- store at 20-25°C (68-77°F)

Inactive ingredients

butyrospermum parkii (shea butter), C18-22 hydroxyalkyl hydroxypropyl guar, calendula officinalis extract, cantharis vesicatoria extract, echinacea angustifolia extract, ethyl alcohol, hydrogenated polydecene, isopropyl myristate, lanolin, lanolin alcohol, petrolatum, phenoxyethanol, water, sodium hydroxide, sodium polyacryloyldimethyl taurate, trideceth-10

Questions or Comments?

1-888-565-2876
Monday through Friday, 9am-5pm EST

Distributed by:
Welmedix Consumer Healthcare
Princeton, NJ 08540

PRINCIPAL DISPLAY PANEL - 21 g Tube Box

NEW &
IMPROVED!

First°Degree®

MAXIMUM STRENGTH
BURN CREAM
PRAMOXINE HCL 1% PAIN RELIEVING CREAM

FAST RELIEF FOR
PAIN + ITCH

- GREAT FOR
  MINOR
  BURNS
  BUG
  BITES
- HELPS REDUCE THE APPEARANCE OF SCARS
- ENRICHED WITH NOURISHING BOTANICALS

1 Tube
Net Wt 3/4 oz (21 g)